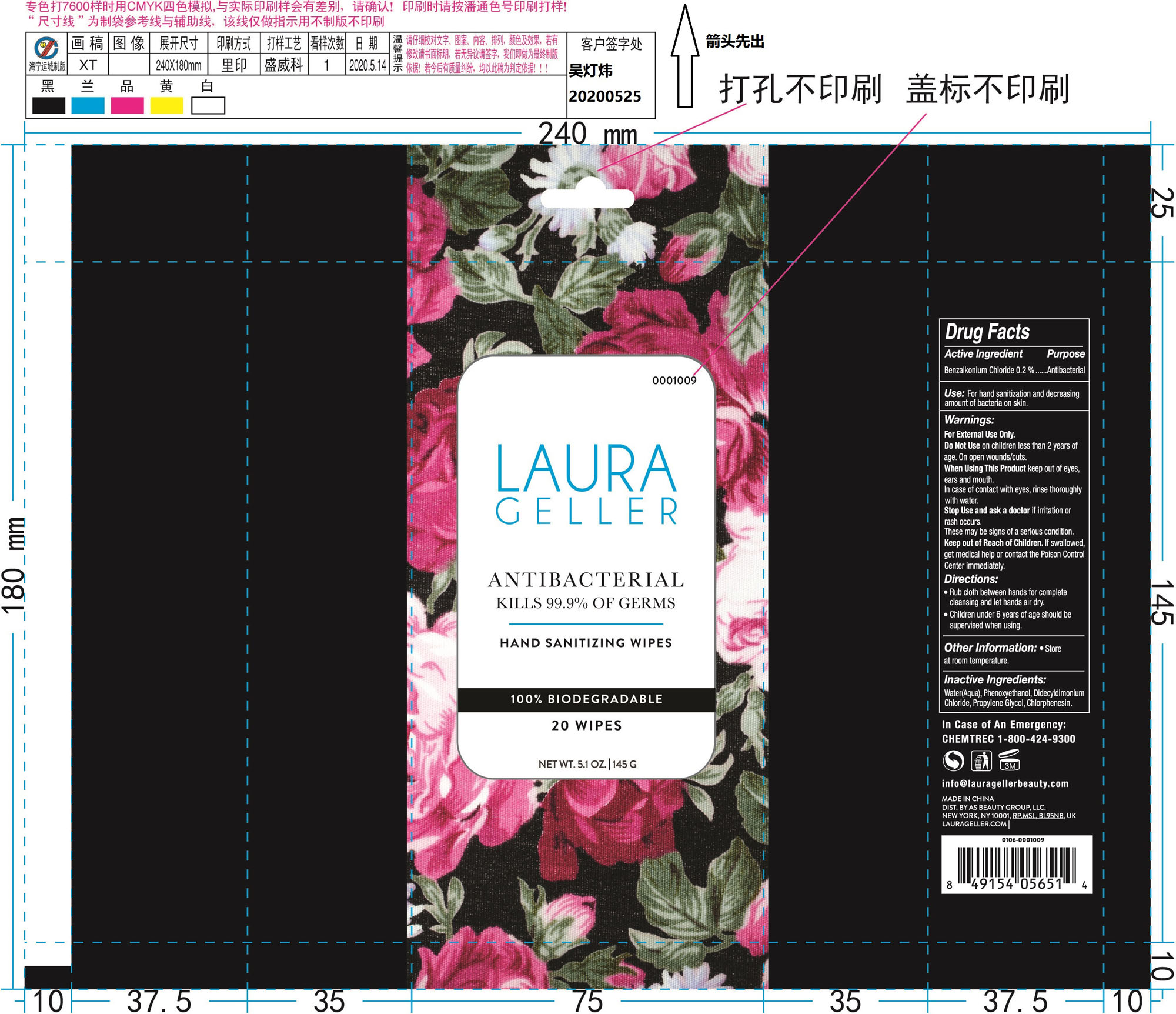 DRUG LABEL: LAURA GELLER antibacterial hand sanitizing wipes
NDC: 76635-220 | Form: CLOTH
Manufacturer: Hangzhou Glamcos Biotech CO.,LTD
Category: otc | Type: HUMAN OTC DRUG LABEL
Date: 20231123

ACTIVE INGREDIENTS: BENZALKONIUM CHLORIDE 0.2 g/100 g
INACTIVE INGREDIENTS: CHLORPHENESIN; DIDECYLDIMONIUM CHLORIDE; WATER; PROPYLENE GLYCOL; PHENOXYETHANOL

Active Ingredient

Benzalkonium Chloride 0.2%

Purpose

Antibacterial

Use

For hand sanitization and decreasing amount of bacteria on skin.

Warnings

For External Use Only.
Do Not Use on children less than 2 years of age.
On open wounds/cuts.
When Using This Product keep out of eyes,ears and mouth.In case of contact with eyes,rinse thoroughly with water.
Stop use and ask a doctor if irritation or rash occurs.These may be signs of a serious condition.

Keep out of reach of children. If swallowed,get medical help or contact the poison control center immediately.

Directions

Rub cloth between hands for complete cleansing and let hands air dry.
Children under 6 years of age should be supervised when using.

Inactive Ingredients

Water, Phenoxyethanol, Didecylmdimonium Chloride, Propylene Glycol, Chlophenesin